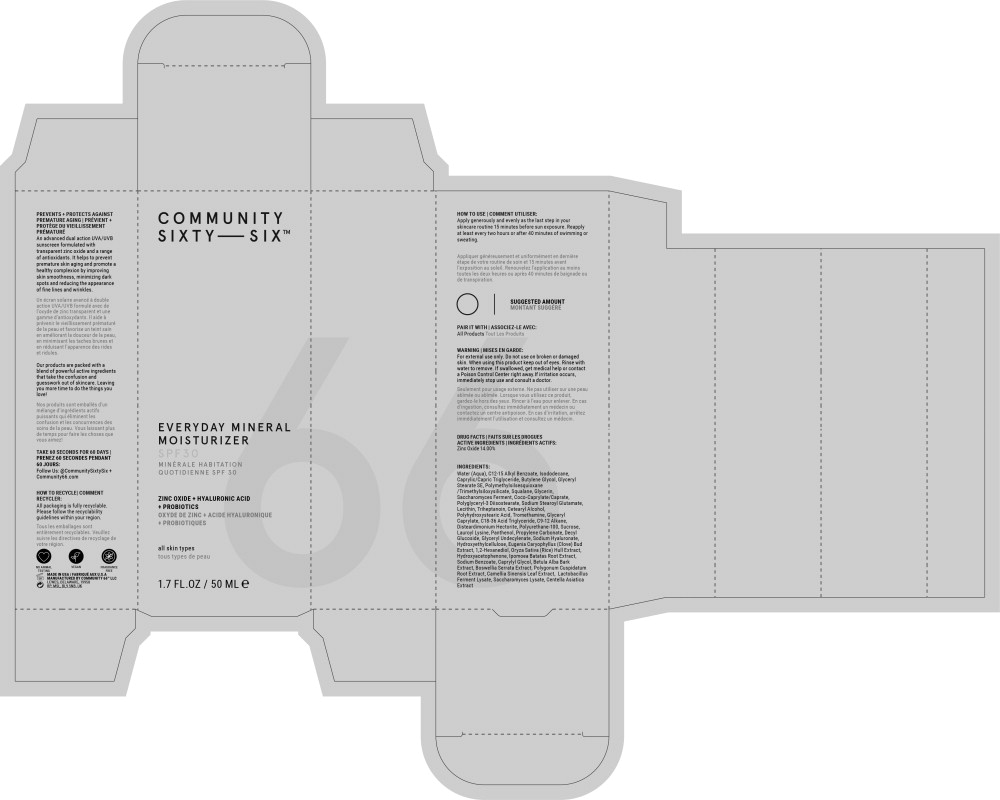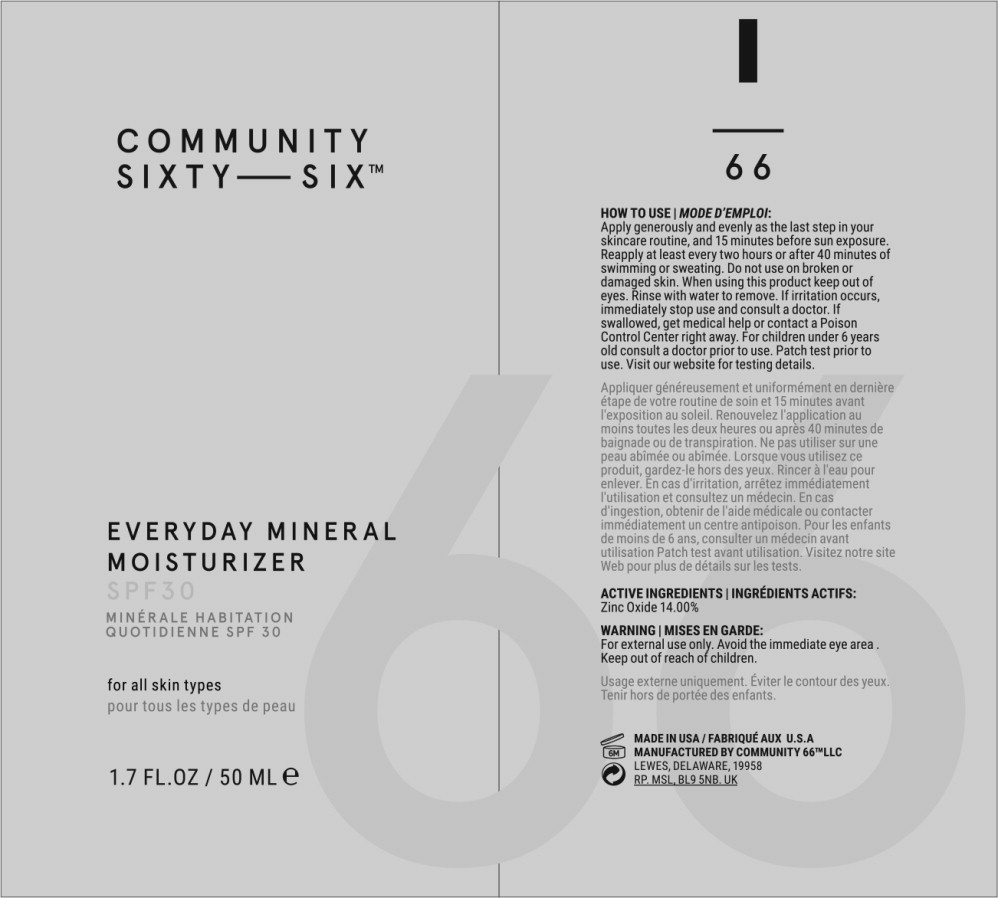 DRUG LABEL: Everyday Mineral Moisturizer SPF 30
NDC: 82769-100 | Form: LOTION
Manufacturer: Community 66, LLC
Category: otc | Type: HUMAN OTC DRUG LABEL
Date: 20220628

ACTIVE INGREDIENTS: Zinc Oxide 136 mg/1 mL
INACTIVE INGREDIENTS: Water; Alkyl (C12-15) Benzoate; Isododecane; Medium-Chain Triglycerides; Butylene Glycol; Glyceryl Stearate SE; Polymethylsilsesquioxane/Trimethylsiloxysilicate; Squalane; Glycerin; Cocoyl Caprylocaprate; Polyglyceryl-3 Diisostearate; Sodium Stearoyl Glutamate; Lecithin, Soybean; Triheptanoin; Cetostearyl Alcohol; Polyhydroxystearic Acid (2300 MW); Tromethamine; Glyceryl Monocaprylate; C18-36 Acid Triglyceride; Disteardimonium Hectorite; Sucrose; Lauroyl Lysine; Panthenol; Polysorbate 20; Propylene Carbonate; Decyl Glucoside; Glyceryl 1-Undecylenate; Hyaluronate Sodium; Hydroxyethyl Cellulose, Unspecified; Clove; 1,2-Hexanediol; Rice Germ; Hydroxyacetophenone; Sweet Potato; Sodium Benzoate; Caprylyl Glycol; Betula Pubescens Bark; Indian Frankincense; Reynoutria Japonica Leaf; Green Tea Leaf; Sodium Phosphate, Dibasic, Anhydrous; Polysorbate 60; Saccharomyces Lysate; Centella Asiatica Whole; Citric Acid Monohydrate; Sodium Phosphate

HOW TO USE | COMMENT UTILISER:

Apply generously and evenly as the last step in your skincare routine 15 minutes before sun exposure. Reapply at least every two hours or after 40 minutes of swimming or sweating.

Appliquer généreusement et uniformément en dernière étape de votre routine de soin et 15 minutes avant l'exposition au soleil. Renouvelez l'application au moins toutes les deux heures ou après 40 minutes de baignade ou de transpiration.

SUGGESTED AMOUNT

MONTANT SUGGÉRÉ

PAIR IT WITH | ASSOCIEZ-LE AVEC:

All Products Tout Les Produits

WARNING | MISES EN GARDE:

For external use only.

Do not use on broken or damaged skin.

When using this product keep out of eyes. Rinse with water to remove. If swallowed, get medical help or contact a Poison Control Center right away. If irritation occurs, immediately stop use and consult a doctor.

Seulement pour usage externe. Ne pas utiliser sur une peau abîmée ou abîmée. Lorsque vous utilisez ce produit, gardez-le hors des yeux. Rincer à l'eau pour enlever. En cas d'ingestion, consultez immédiatement un médecin ou contactez un centre antipoison. En cas d'irritation, arrêtez immédiatement l'utilisation et consultez un médecin.

DRUG FACTS | FAITS SUR LES DROGUES

ACTIVE INGREDIENTS | INGRÉDIENTS ACTIFS:

Zinc Oxide 14.00%

INGREDIENTS:

Water (Aqua), C12-15 Alkyl Benzoate, Isododecane, Caprylic/Capric Triglyceride, Butylene Glycol, Glyceryl Stearate SE, Polymethylsilsesquioxane /Trimethylsiloxysilicate, Squalane, Glycerin, Saccharomyces Ferment, Coco-Caprylate/Caprate, Polyglyceryl-3 Diisostearate, Sodium Stearoyl Glutamate, Lecithin, Triheptanoin, Cetearyl Alcohol, Polyhydroxystearic Acid, Tromethamine, Glyceryl Caprylate, C18-36 Acid Triglyceride, C9-12 Alkane, Disteardimonium Hectorite, Polyurethane-100, Sucrose, Lauroyl Lysine, Panthenol, Propylene Carbonate, Decyl Glucoside, Glyceryl Undecylenate, Sodium Hyaluronate, Hydroxyethylcellulose, Eugenia Caryophyllus (Clove) Bud Extract, 1,2-Hexanediol, Oryza Sativa (Rice) Hull Extract, Hydroxyacetophenone, Ipomoea Batatas Root Extract, Sodium Benzoate, Caprylyl Glycol, Betula Alba Bark Extract, Boswellia Serrata Extract, Polygonum Cuspidatum Root Extract, Camellia Sinensis Leaf Extract, Lactobacillus Ferment Lysate, Saccharomyces Lysate, Centella Asiatica Extract

Principal Display Panel – 50 mL Carton Label

COMMUNITY
SIXTY – SIX™

EVERYDAY MINERAL
MOISTURIZER

SPF 30

MINÉRALE HABITATION

QUOTIDIENNE SPF 30

ZINC OXIDE + HYALURONIC ACID
+ PROBIOTICS

OXYDE DE ZINC + ACIDE HYALURONIQUE
+ PROBIOTIQUES

all skin types

tous types de peau

1.7 FL.OZ / 50 ML ℮

Principal Display Panel – 50 mL Bottle Label

COMMUNITY
SIXTY – SIX™

EVERYDAY MINERAL
MOISTURIZER

SPF 30

MINÉRALE HABITATION

QUOTIDIENNE SPF 30

1.7 FL.OZ / 50 ML ℮